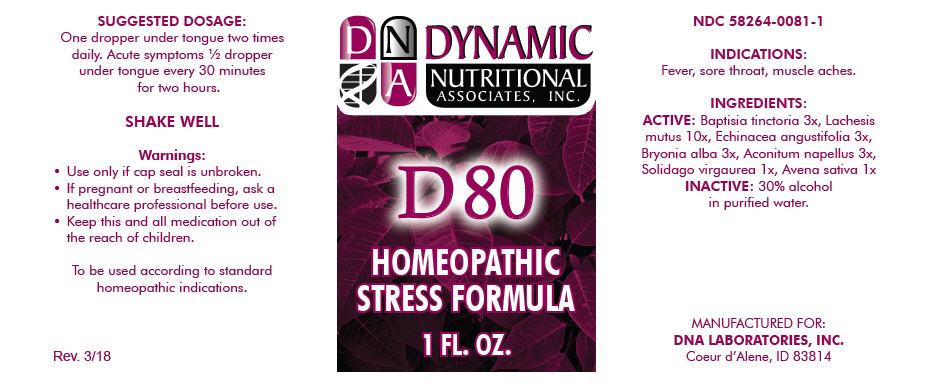 DRUG LABEL: D-80
NDC: 58264-0081 | Form: SOLUTION
Manufacturer: DNA Labs, Inc.
Category: homeopathic | Type: HUMAN OTC DRUG LABEL
Date: 20250113

ACTIVE INGREDIENTS: BAPTISIA TINCTORIA ROOT 3 [hp_X]/1 mL; LACHESIS MUTA VENOM 10 [hp_X]/1 mL; ECHINACEA ANGUSTIFOLIA 3 [hp_X]/1 mL; BRYONIA ALBA ROOT 3 [hp_X]/1 mL; ACONITUM NAPELLUS 3 [hp_X]/1 mL; SOLIDAGO VIRGAUREA FLOWERING TOP 1 [hp_X]/1 mL; AVENA SATIVA FLOWERING TOP 1 [hp_X]/1 mL
INACTIVE INGREDIENTS: ALCOHOL; WATER

D-80

NDC 58264-0081-1

INDICATIONS

PURPOSE

Fever, sore throat, muscle aches.

INGREDIENTS

ACTIVE

Baptisia tinctoria 3x, Lachesis mutus 10x, Echinacea angustifolia 3x, Bryonia alba 3x, Aconitum napellus 3x, Solidago virgaurea 1x, Avena sativa 1x

INACTIVE

30% alcohol in purified water.

SUGGESTED DOSAGE

One dropper under tongue two times daily. Acute symptoms ½ dropper under tongue every 30 minutes for two hours.

STORAGE AND HANDLING

SHAKE WELL

Warnings

- Use only if cap seal is unbroken.

PREGNANCY OR BREAST FEEDING

- If pregnant or breastfeeding, ask a healthcare professional before use.

KEEP OUT OF REACH OF CHILDREN

- Keep this and all medication out of the reach of children.

To be used according to standard homeopathic indications.

PRINCIPAL DISPLAY PANEL - 1 FL. OZ. Bottle Label

DYNAMIC
NUTRITIONAL
ASSOCIATES, INC.

D 80

HOMEOPATHIC
STRESS FORMULA

1 FL. OZ.